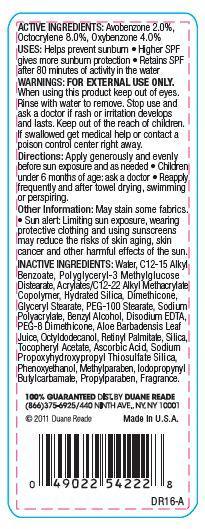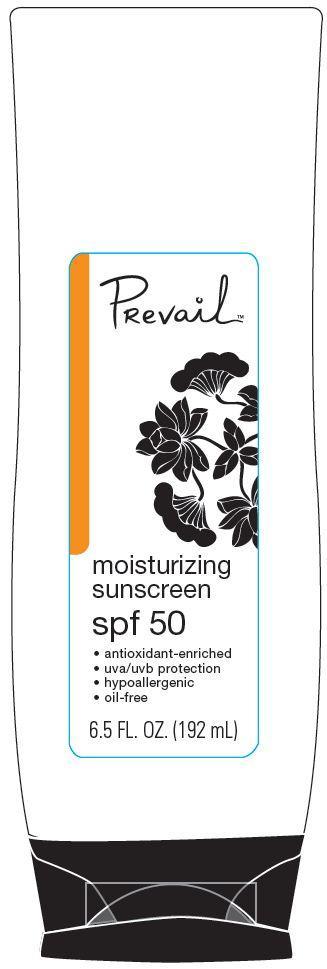 DRUG LABEL: Duane Reade Prevail Moisturizing Sunscreen
NDC: 67732-412 | Form: LOTION
Manufacturer: DUANE READE INC.
Category: otc | Type: HUMAN OTC DRUG LABEL
Date: 20121114

ACTIVE INGREDIENTS: AVOBENZONE 2 g/100 g; OCTOCRYLENE 8 g/100 g; OXYBENZONE 4 g/100 g
INACTIVE INGREDIENTS: WATER; ALKYL (C12-15) BENZOATE; DIMETHICONE; GLYCERYL MONOSTEARATE; HYDRATED SILICA; PEG-100 STEARATE; SODIUM POLYACRYLATE (2500000 MW); BENZYL ALCOHOL; PHENOXYETHANOL; EDETATE DISODIUM; IODOPROPYNYL BUTYLCARBAMATE; PEG-8 DIMETHICONE; ALOE VERA LEAF; OCTYLDODECANOL; VITAMIN A PALMITATE; SILICON DIOXIDE; .ALPHA.-TOCOPHEROL ACETATE; ASCORBIC ACID; METHYLPARABEN; PROPYLPARABEN

ACTIVE INGREDIENTS:

Avobenzone 2.0 %

Octocrylene 8.0 %

Oxybenzone 4.0%

Purpose

Sunscreen

USES:

- Helps prevent sunburn
- Higher SPF gives more sunburn protection
- Retains SPF after 80 minutes of activity in the water

WARNINGS:

FOR EXTERNAL USE ONLY.

When using this product

keep out of eyes. Rinse with water to remove.

stop use and ask a doctor if

rash or irritation develops and lasts

KEEP OUT OF REACH OF CHILDREN

keep out of the reach of children. If swallowed get medical help or contact a poison control center right away.

Directions:

- Apply generously and evenly before sun exposure and as needed
- Children under 6 months of age:ask a doctor
- Reapply frequently after towel drying, swimming or perspiring.

Other Information

May stain some fabrics.

- Sun Alert: Limiting sun exposure, wearing, protective clothing, and using sunscreens may reduce the risks of skin aging, skin cancer, and other harmful effects of the sun.

INACTIVE INGREDIENTS:

Water, C12-15 Alkyl Benzoate, Polyglyceryl-3 Methylglucose Distearate, Acrylates/C12-22 Alkyl methacrylate Copolymer, Hydrated Silica, Dimethicone, Glyceryl Stearate, PEG_100 Stearate, Sodium Polyacrylate, Benzyl Alcohol, Disodium EDTA, PEG_8 Dimethicone, Aloe Barbadensis leaf Juice, Octyldodecanol, Retinyl Palmitate, Silica, Tocopheryl Acetate, Ascorbic Acid, Sodium Propoxyhydroxypropyl Thiosulfate Silica, Phenoxyethanol, Methylparaben, Iodopropynyl Butylcarbamate, Propylparaben, Fragrance.

Principal Display Panel

PRevail

moisturizing sunscreen

spf 50

- antioxidant-enriched
- uva/uvb protection
- hypoallergic
- oil-free

6.5 FL. OZ. (192 mL)